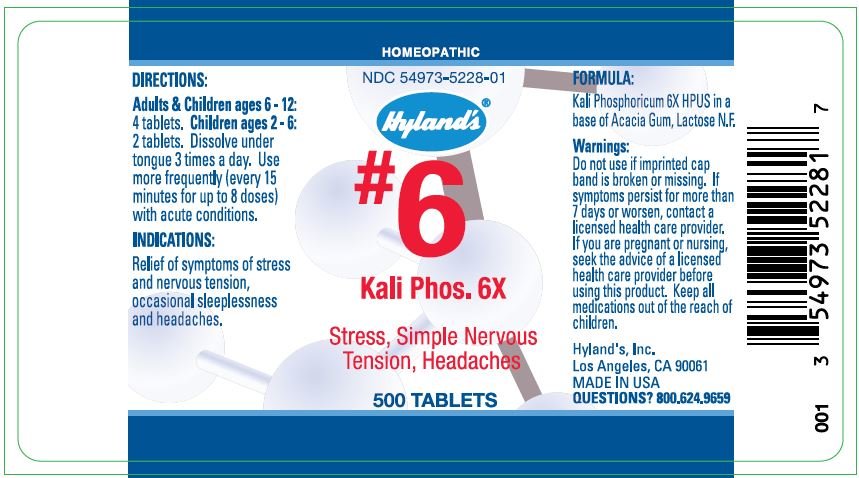 DRUG LABEL: KALI PHOS
NDC: 54973-5228 | Form: TABLET
Manufacturer: Hyland's Inc.
Category: homeopathic | Type: HUMAN OTC DRUG LABEL
Date: 20221219

ACTIVE INGREDIENTS: POTASSIUM PHOSPHATE, UNSPECIFIED FORM 6 [hp_X]/1 1
INACTIVE INGREDIENTS: ACACIA; LACTOSE

KALI PHOS. 6X

DIRECTIONS

Adults & Children ages 6 - 12: 4 tablets. Children ages 2 - 6: 2 tablets. Dissolve under tongue 3 times a day. Use more frequently (every 15 minutes for up to 8 doses) with acute conditions.

INDICATIONS

PURPOSE

Relief of symptoms of stress and nervous tension, occasional sleeplessness and headaches.

FORMULA

Kali Phosphoricum 6X HPUS

INACTIVE INGREDIENT

in a base of Acacia Gum, Lactose N.F.

Warnings

Do not use if imprinted cap band is broken or missing.

ASK DOCTOR

If symptoms persist for more than 7 days or worsen, contact a licensed health care provider.

PREGNANCY OR BREAST FEEDING

If you are pregnant or nursing, seek the advice of a licensed health care provider before using this product.

KEEP OUT OF REACH OF CHILDREN

Keep all medications out of the reach of children.

QUESTIONS?

800.624.9659

PRINCIPAL DISPLAY PANEL - 500 Tablet Bottle Label

HOMEOPATHIC

NDC 54973-5228-01

Hyland's®

#6
Kali Phos. 6X

Stress, Simple Nervous
Tension, Headaches

500 TABLETS